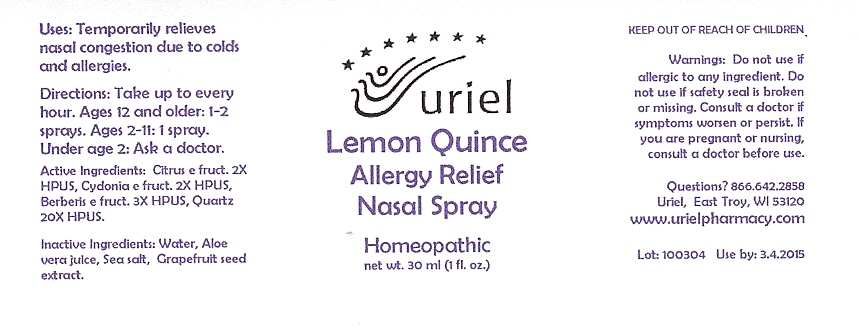 DRUG LABEL: Lemon Quince Allergy Relief
NDC: 48951-6024 | Form: SPRAY
Manufacturer: Uriel Pharmacy Inc
Category: homeopathic | Type: HUMAN OTC DRUG LABEL
Date: 20100316

ACTIVE INGREDIENTS: LEMON 2 [hp_X]/1 1; CHINESE QUINCE EXTRACT 2 [hp_X]/1 1; BERBERIS VULGARIS FRUIT 3 [hp_X]/1 1; SILICON DIOXIDE 20 [hp_X]/1 1
INACTIVE INGREDIENTS: WATER; ALOE VERA LEAF; SODIUM CHLORIDE; GRAPEFRUIT SEED

Lemon Quince Allergy Relief Nasal Spray- 1 oz.

Purpose

Uses: Temporarily relieves nasal congestion due to colds and allergies.

Dosage & Administration

Directions: Take up to every hour. Ages 12 and older: 1-2 sprays. Ages 2-11: 1 spray. Under age 2: Ask a doctor.

OTC-Active Ingredient

Active Ingredients: Citrus e fruct. 2X HPUS, Cydonia e fruct. 2X HPUS, Berberis e fruct. 3X HPUS, Quartz 20X HPUS.

Inactive Ingredient

Inactive Ingredients: Water, Aloe vera juice, Sea salt, Grapefruit seed extract.

Keep out of reach of children

Do not use section

Warnings: Do not use if allergic to any ingredient. Do not use if safety seal is broken or missing.

Ask doctor section

Consult a doctor if symptoms worsen or persist.

Pregnancy or breast feeding section

If you are pregnant or nursing, consult a doctor before use.

Questions section

Questions? Uriel Pharmacy

866 642-2858 East Troy, WI 53120

www.urielpharmacy.com

Principal Display Panel

Lemon Quince

Allergy Relief

Nasal Spray

Homeopathic

net wt. 30 ml (1 fl. oz.)